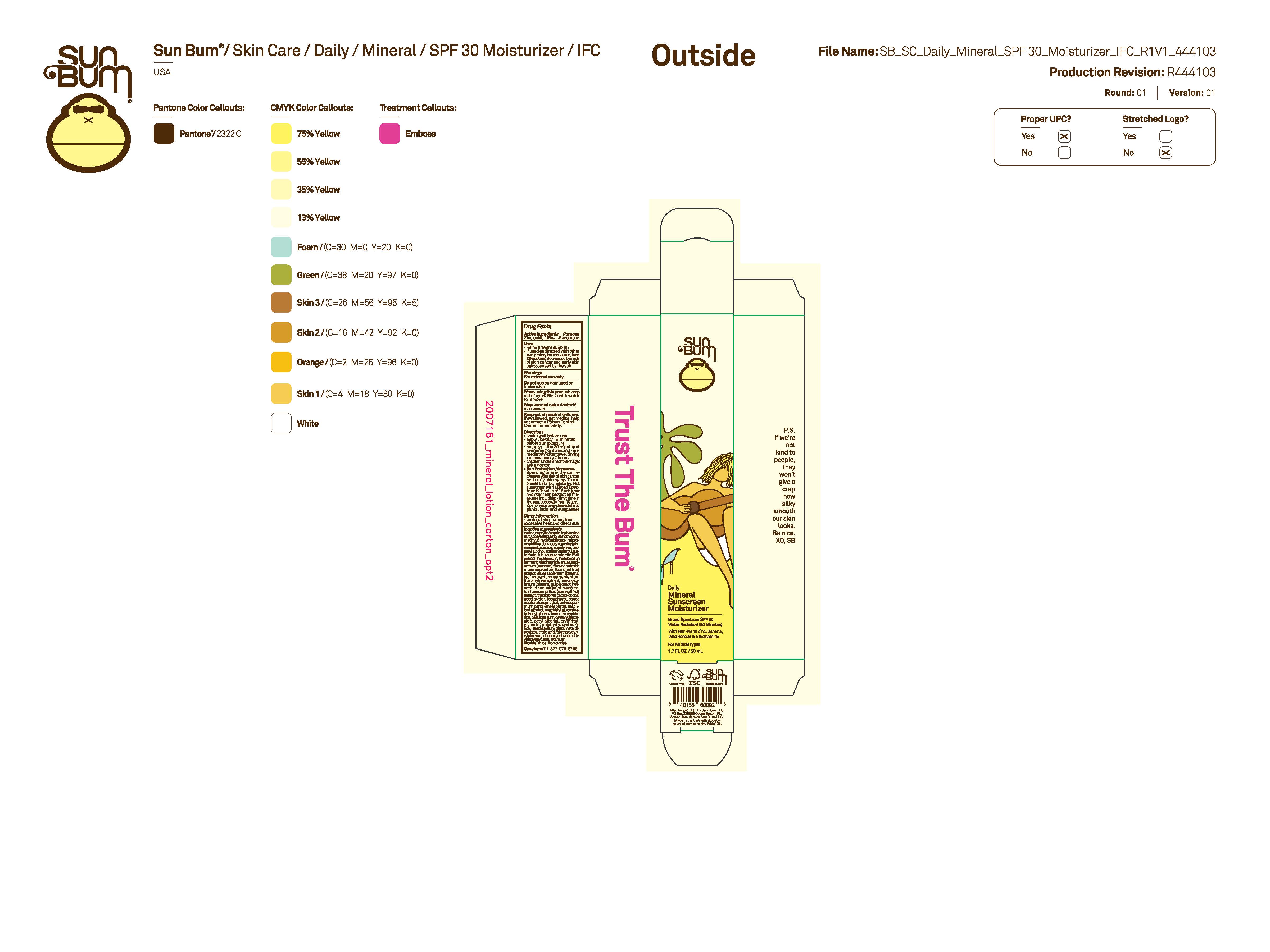 DRUG LABEL: Sun Bum Daily Mineral Sunscreen Moisturizer Broad Spectrum SPF 30
NDC: 69039-761 | Form: LOTION
Manufacturer: Sun Bum, LLC
Category: otc | Type: HUMAN OTC DRUG LABEL
Date: 20250818

ACTIVE INGREDIENTS: ZINC OXIDE 150 mg/1 mL
INACTIVE INGREDIENTS: BUTYROSPERMUM PARKII (SHEA) BUTTER; WATER; ARACHIDYL ALCOHOL; ARACHIDYL GLUCOSIDE; BEHENYL ALCOHOL; CETEARYL GLUCOSIDE; MICA; BANANA; HELIANTHUS ANNUUS FLOWERING TOP; COCOS NUCIFERA (COCONUT) OIL; CAPRYLIC/CAPRIC TRIGLYCERIDE; CELLULOSE GUM; BISMUTH OXYCHLORIDE; HIBISCUS SABDARIFFA WHOLE; CAPRYLOYL GLYCERIN/SEBACIC ACID COPOLYMER (2000 MPA.S); LACTOBACILLUS; MUSA X PARADISIACA FLOWER; FERROUS OXIDE; PHENOXYETHANOL; TRIETHOXYCAPRYLYLSILANE; COCOS NUCIFERA (COCONUT) FRUIT; CETYL ALCOHOL; BANANA LEAF; BANANA PEEL; DIMETHICONE; ETHYLHEXYLGLYCERIN; NIACINAMIDE; GLYCERIN; SODIUM STEAROYL GLUTAMATE; TOCOPHEROL; TETRASODIUM GLUTAMATE DIACETATE; CITRIC ACID; TITANIUM DIOXIDE; MICROCRYSTALLINE CELLULOSE; BUTYLOCTYL SALICYLATE; METHYL DIHYDROABIETATE; THEOBROMA CACAO (COCOA) SEED BUTTER; POLYHYDROXYSTEARIC ACID (2300 MW); ERYTHRITOL; CETEARYL ALCOHOL

Sun Bum Daily Mineral Sunscreen Moisturizer Broad Spectrum SPF 30

Active Ingredients

Zinc Oxide: 15%

Purpose

Sunscreen

Uses

• helps prevent sunburn • if used as directed with other sun protection measures, (see Directions) decreases the risk of skin cancer and early skin aging caused by the sun

Warnings

For external use only

Do not use on damaged or broken skin

When using this product keep out of eyes. Rinse with water to remove.

Stop use and ask a doctor if rash occurs

Keep out of reach of children. If swallowed, get medical help or contact a Poison Control Center immediately.

Warnings

Keep Out Of Reach Of Children

Directions

• shake well before use

• apply liberally 15 minutes before sun exposure

• reapply: • after 80 minutes of swimming or sweating • immediately after towel drying • at least every 2 hours

• children under 6 months of age: ask a doctor

• Sun Protection Measures. Spending time in the sun increases your risk of skin cancer and early skin aging. To decrease this risk, regularly use a sunscreen with a Broad Spectrum SPF value of 15 or higher and other sun protection measures including:

• limit time in the sun, especially from 10 a.m.- 2 p.m.

• wear long-sleeved shirts, pants, hats and sunglasses

Directions

• shake well before use

• apply liberally 15 minutes before sun exposure

Other Information

protect this product from excessive heat and direct sun

Inactive Ingredients

Water, Caprylic/Capric Triglyceride, Butyloctyl Salicylate, Dimethicone, Methyl Dihydroabietate, Microcrystalline Cellulose, Capryloyl Glycerin/Sebacic Acid Copolymer, Cetearyl Alcohol, Sodium Stearoyl Glutamate, Hibiscus Sabdariffa Fruit Extract, Lactobacillus, Lactobacillus Ferment, Niacinamide, Musa Sapientum (Banana) Flower Extract, Musa Sapientum (Banana) Fruit Extract, Musa Sapientum (Banana) Leaf Extract, Musa Sapientum (Banana) Peel Extract, Musa Sapientum (Banana) Pulp Extract, Helianthus Annuus (Sunflower) Extract, Cocos Nucifera (Coconut) Fruit Extract, Theobroma Cacao (Cocoa) Seed Butter, Tocopherol, Cocos Nucifera (Coconut) Oil, Butyrospermum Parkii (Shea) Butter, Arachidyl Alcohol, Arachidyl Glucoside, Behenyl Alcohol, Bismuth Oxychloride, Cellulose Gum, Cetearyl Glucoside, Cetyl Alcohol, Erythritol, Glycerin, Polyhydroxystearic Acid, Tetrasodium Glutamate Diacetate, Citric Acid, Triethoxycaprylylsilane, Phenoxyethanol, Ethylhexylglycerin, Titanium Dioxide, Mica, Iron Oxides

Questions?

1-877-978-6286